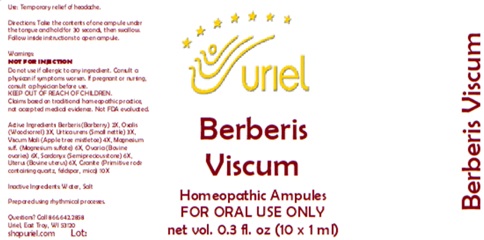 DRUG LABEL: Berberis Viscum
NDC: 48951-2058 | Form: LIQUID
Manufacturer: Uriel Pharmacy Inc.
Category: homeopathic | Type: HUMAN OTC DRUG LABEL
Date: 20251114

ACTIVE INGREDIENTS: BERBERIS VULGARIS ROOT BARK 2 [hp_X]/1 mL; OXALIS ACETOSELLA LEAF 3 [hp_X]/1 mL; URTICA URENS 3 [hp_X]/1 mL; VISCUM ALBUM FRUITING TOP 4 [hp_X]/1 mL; MAGNESIUM SULFATE, UNSPECIFIED 6 [hp_X]/1 mL; BOS TAURUS OVARY 6 [hp_X]/1 mL; ALUMINUM OXIDE 6 [hp_X]/1 mL; BOS TAURUS UTERUS 6 [hp_X]/1 mL; PENOXSULAM 10 [hp_X]/1 mL
INACTIVE INGREDIENTS: WATER; SODIUM CHLORIDE; LACTOSE, UNSPECIFIED FORM

Berberis Viscum

PURPOSE

Use: Temporary relief of headache.

INDICATIONS AND USAGE

FOR ORAL USE ONLY

DOSAGE AND ADMINISTRATION

Directions: Take the contents of one ampule under the tongue and hold for 30 seconds, then swallow. Follow inside instructions to open ampule.

Warnings:
NOT FOR INJECTION
Do not use if allergic to any ingredient. Consult a physican if symptoms worsen. If pregnant or nursing, consult a physician before use.
Claims based on traditional homeopathic practice, not accepted medical evidence. Not FDA evaluated

KEEP OUT OF REACH OF CHILDREN.

ACTIVE INGREDIENT

Active Ingredients: Berberis (Barberry) 2X, Oxalis (Wood sorrel) 3X, Urtica urens (Small nettle) 3X, Viscum Mali (Apple tree mistletoe) 4X, Magnesium sulf. (Magnesium sulfate) 6X, Ovaria (Bovine ovaries) 6X, Sardonyx (Semiprecious stone) 6X, Uterus (Bovine uterus) 6X, Granite (Primitive rock containing quartz, feldspar, mica) 10X

Inactive Ingredients: Water, Salt

Prepared using rhythmical processes.

Questions? Call 866.642.2858
Uriel, East Troy, WI 53120
shopuriel.com Lot: